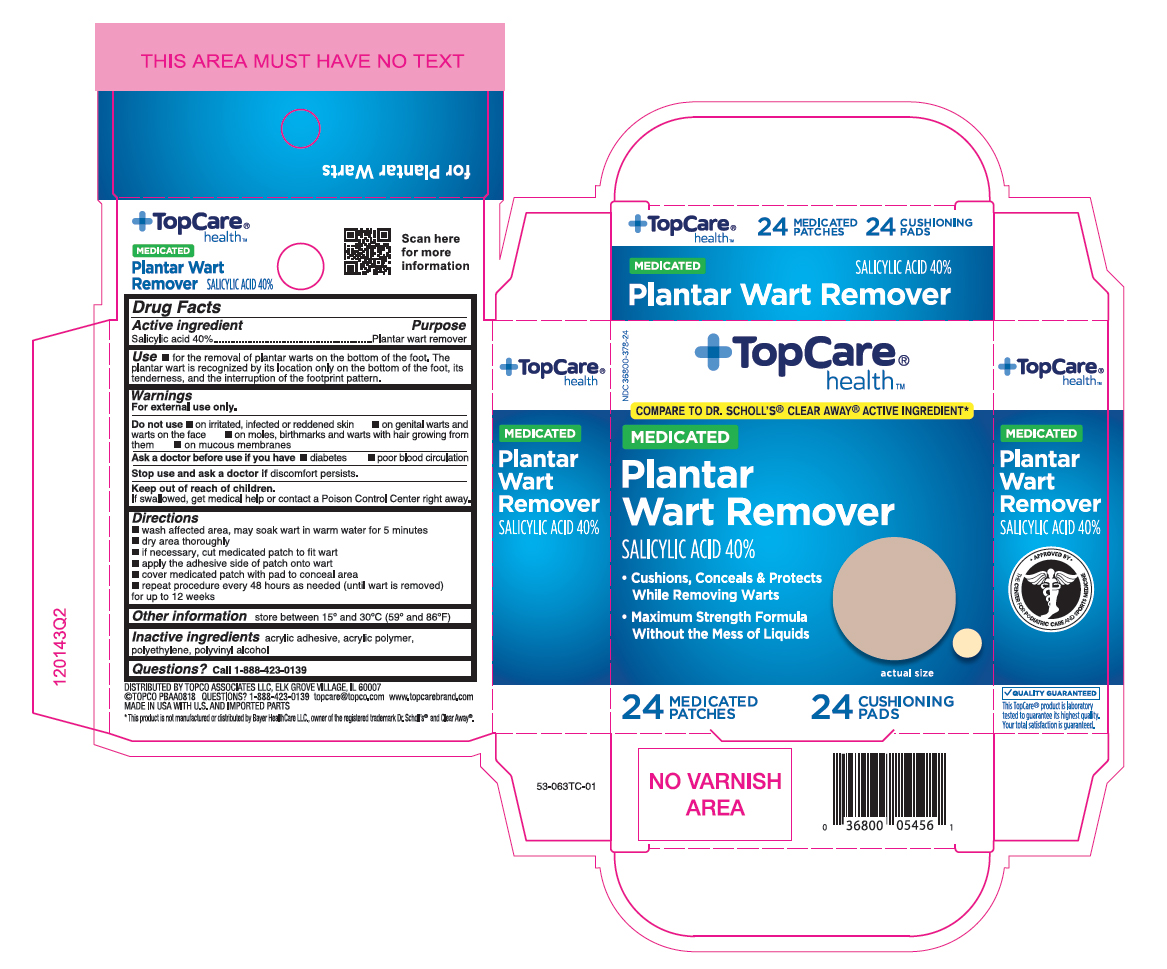 DRUG LABEL: Salicylic Acid
NDC: 36800-378 | Form: PATCH
Manufacturer: Topco Associates LLC
Category: otc | Type: HUMAN OTC DRUG LABEL
Date: 20260115

ACTIVE INGREDIENTS: SALICYLIC ACID 40 mg/24 1
INACTIVE INGREDIENTS: POLYVINYL ALCOHOL; HIGH DENSITY POLYETHYLENE

Medicated Plantar Wart Remover

Active ingredient

Salicylic acid 40%

Purpose

Plantar wart remover

Uses

- for the removal of plantar warts on the bottom of the foot. The plantar wart is recognized by its location only on the bottom of the foot, its tenderness, and the interruption of the footprint pattern.

Warnings

For external use only.

Do not use

- on irritated, infected or reddened skin
- on genital warts and warts on the face
- on moles, birthmarks and warts with hair growing from them
- on mucous membranes

Ask a doctor before use if you ahve

- diabetes
- poor blood circulation

Stop use and ask a doctor

if discomfort persists.

Keep out of the reach of children.

If swallowed, get medical help or contact a Poison Control Center right away.

Directions

- wash affected area, may soak wart in warm water for 5 minutes
- dry area thoroughly
- if necessary, cut medicated patch to fit wart
- apply the adhesive side of patch onto wart
- cover medicated patch with pad to conceal area
- repeat procedure every 48 hours as needed (until wart is removed) for up to 12 weeks

Other information

store between 15° and 30°C (59° and 86°F)

Inactive ingredients

acrylic adhesive, acrylic polymer, polyethylene, polyvinyl alcohol

Questions?

Call 1-888-423-0139

Principal Display Panel

TopCare

health

MEDICATED

Plantar

Wart Remover

SALICYLIC ACID 40%

- Cushions, Conceals & Protects While Removing Warts
- Maximum Strength Formula Without the Mess of Liquids

24 MEDICATED PATCHES 24 CUSHIONING PADS